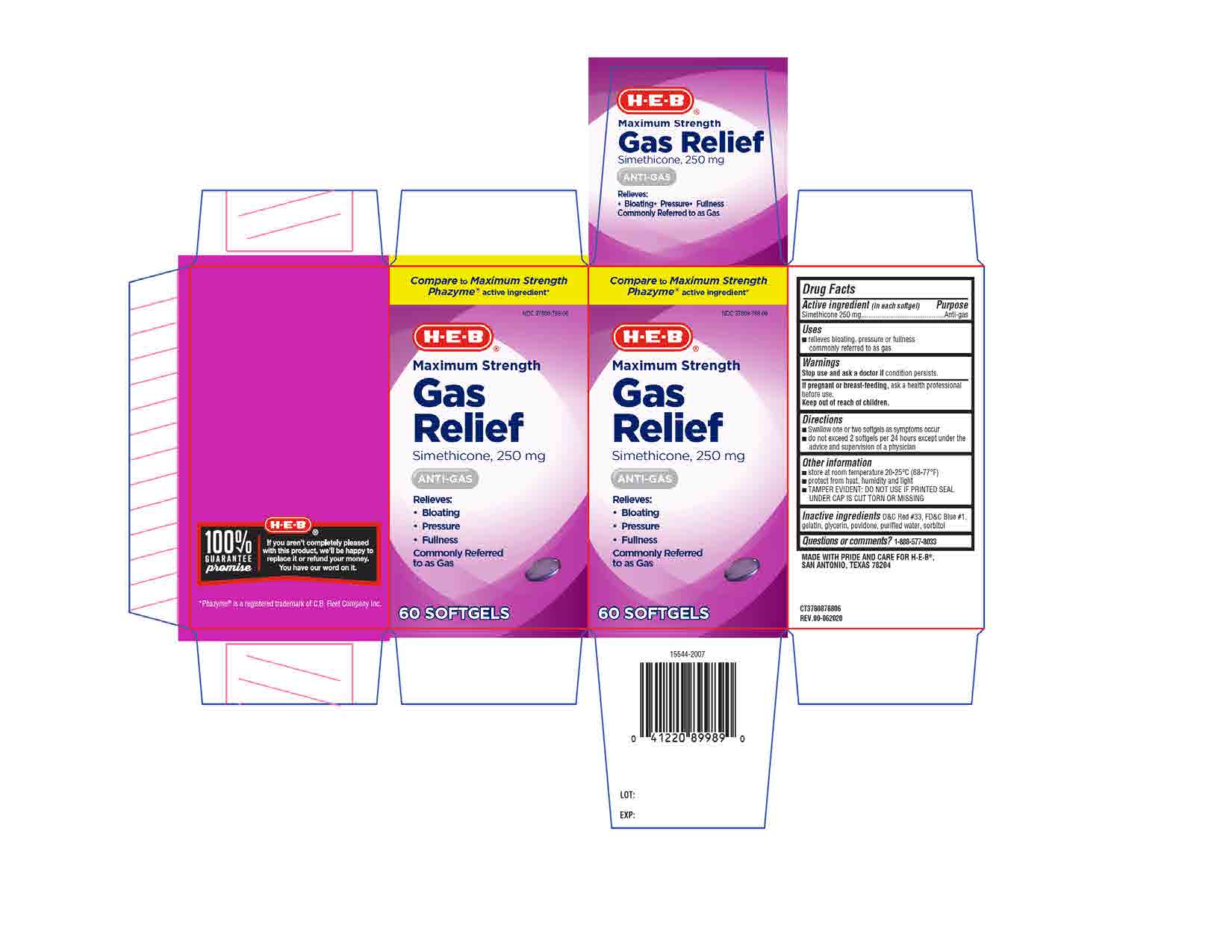 DRUG LABEL: Simethicone
NDC: 37808-788 | Form: CAPSULE, LIQUID FILLED
Manufacturer: H-E-B
Category: otc | Type: HUMAN OTC DRUG LABEL
Date: 20201020

ACTIVE INGREDIENTS: DIMETHICONE 250 mg/1 1
INACTIVE INGREDIENTS: WATER; FD&C BLUE NO. 1; SORBITOL; D&C RED NO. 33; GLYCERIN; POVIDONE; GELATIN

MS Gas Relief - Simethicone 250mg

ACTIVE INGREDIENT

Simethicone 250mg

PURPOSE

Anti-gas

INACTIVE INGREDIENT

D&C Red #33, FD&C Blue #1, gelatin, glycerin, povidone, purified water, sorbitol

DOSAGE AND ADMINISTRATION

- swallow one or two softgels as symptoms occur
- do not exceed 2 softgels per 24 hours except under the advice and super vision of a physician

INDICATIONS AND USAGE

relieves bloating, pressure or fullness commonly referred to as gas

Stop use and ask a doctor if condition persists.

If pregnant or breast-feeding, ask a health professional before use.

Keep out of reach of children.

Keep out of reach of children.

OTHER SAFETY INFORMATION

- store at room temperature between 20-25°C (68-77ºF).
- protect from heat, humidity and light.
- TAMPER EVIDENT: DO NOT USE IF PRINTED SEAL UNDER CAP IS CUT TORN OR MISSING